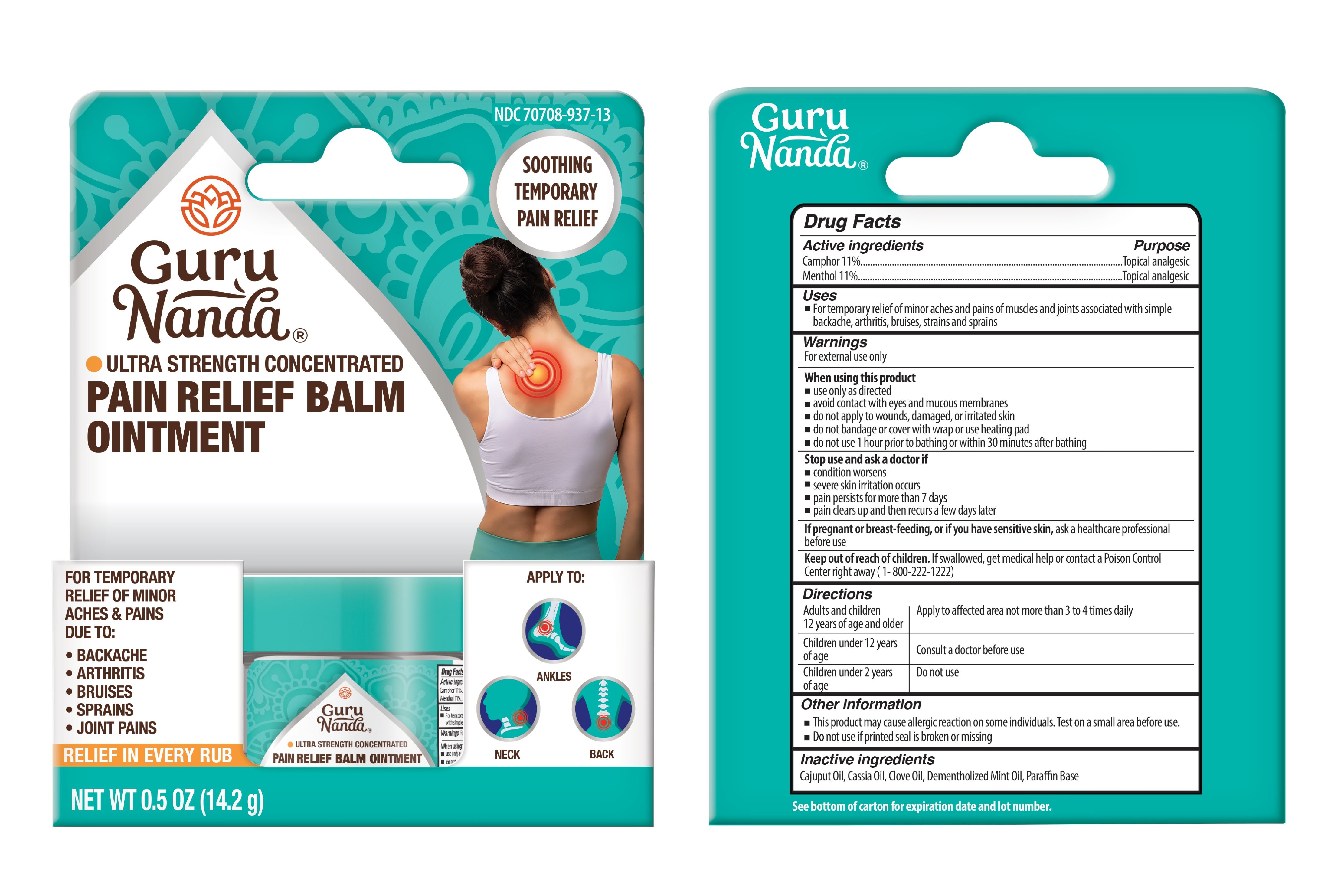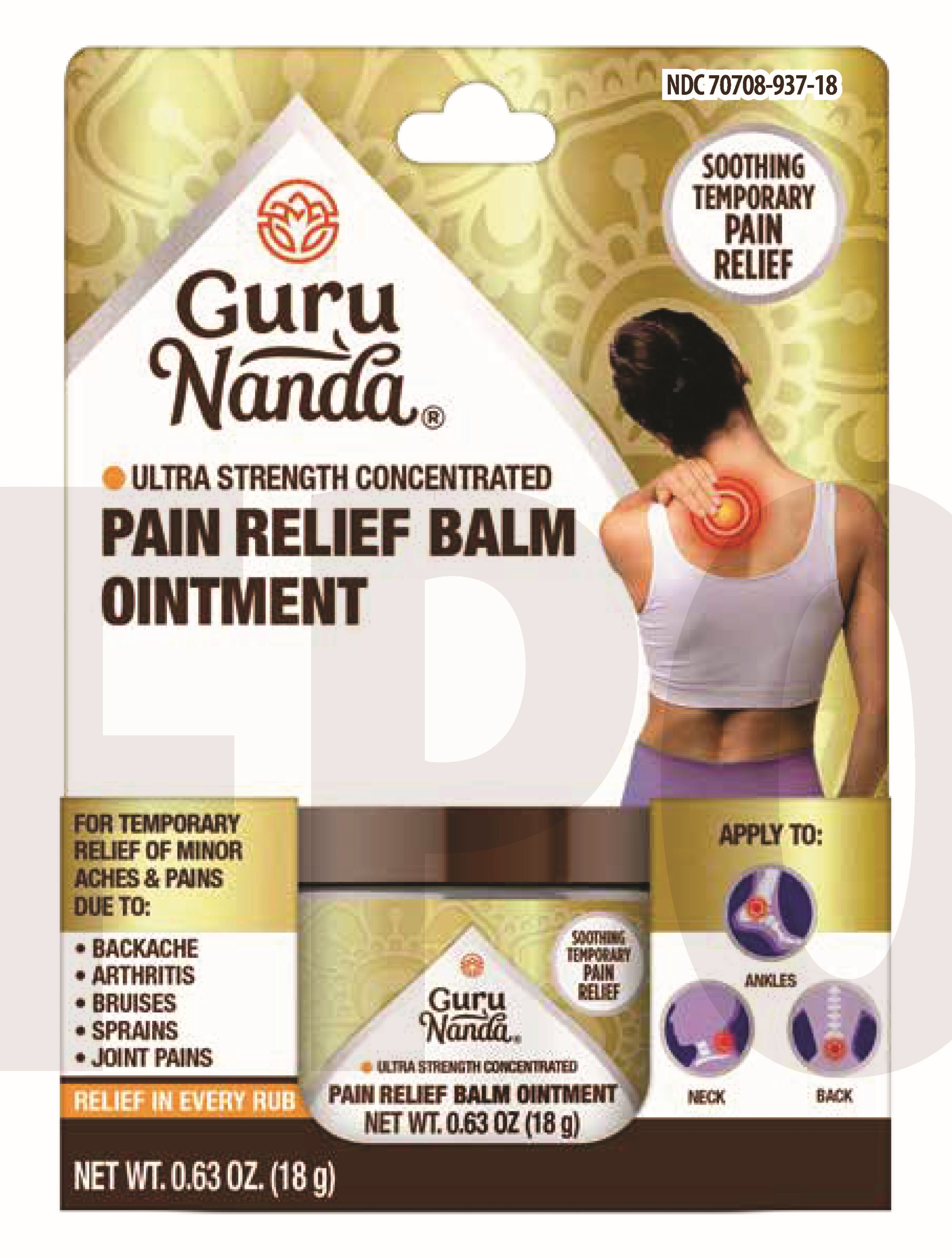 DRUG LABEL: GuruNanda Pain Relief
NDC: 70708-937 | Form: OINTMENT
Manufacturer: GURUNANDA, LLC
Category: otc | Type: HUMAN OTC DRUG LABEL
Date: 20251124

ACTIVE INGREDIENTS: CAMPHOR (SYNTHETIC) 110 mg/1 g; MENTHOL 110 mg/1 g
INACTIVE INGREDIENTS: PEPPERMINT OIL; PARAFFIN; CHINESE CINNAMON OIL; CLOVE OIL; CAJUPUT OIL

GuruNanda Pain Relief Balm Ointment

Active Ingredients

Camphor 11%

Menthol 11%

Purpose

Topical analgesic

Uses

For the temporary relief of minor aches and pains of muscles and joints associated with simple backache, arthirtis, bruises, strains and sprains

Warnings

For external use only.

When using this product

use only as directed, avoid contact with eye and mucous membranes, do not apply to wounds, damaged or irritated skin, do not bandage or cover with wrap or heating pad, do not use 1 hour prior to bathing or within 30 minutes after bathing

Stop use and ask a doctor if

- condition worsens
- severe skin irritaiton occurs
- pain persists for more than 7 days
- pain clears up and then recurs a few days later

If pregnant or breast-feeding, or if you have sensitive skin

ask a healthcare professional before use.

Keep out of reach of children.

If swallowed, get medical help or contact a Poison Control Center immediately (1-800-222-1222).

Directions

- for adults and children over 12 years: rub well on the affected area. Repeat 3 to 4 times daily
- for children 12 years of age or younger: consult a doctor before use
- Children under 2 years of age: Do not use

Other information

This product may cause allergic reaction on some individuals. Test on a small area before use. Do not use if printed seal is broken or missing

Inactive ingredients

Cajuput Oil, Cassia Oil, Clove Oil, Dementholized Mint Oil, Paraffin Base